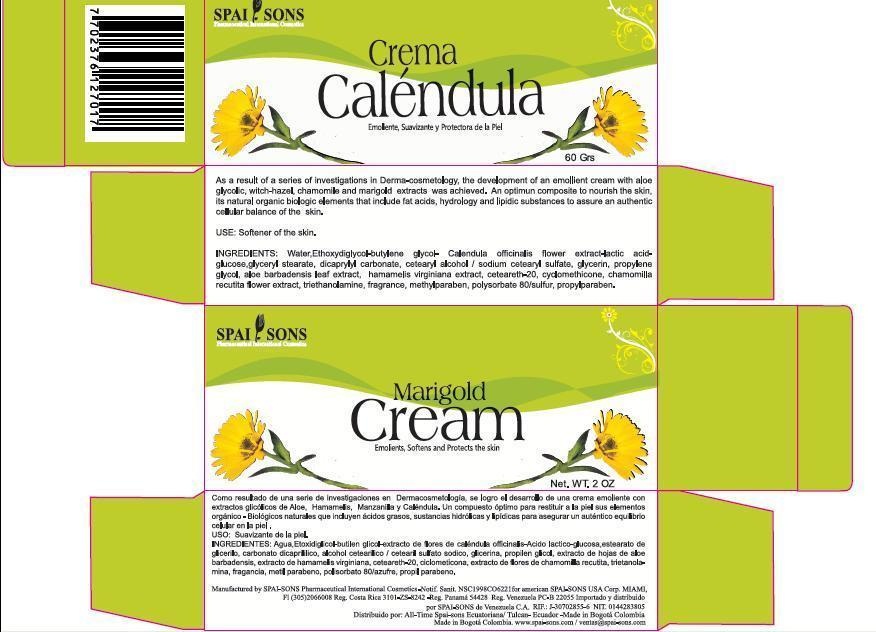 DRUG LABEL: Spai-Sons
NDC: 66854-001 | Form: CREAM
Manufacturer: SPAI SONS PHARMACEUTICAL INTERNATIONAL COSMETICS
Category: otc | Type: HUMAN OTC DRUG LABEL
Date: 20120425

ACTIVE INGREDIENTS: CALENDULA OFFICINALIS FLOWER 20 g/100 g; SULFUR 0.11 g/100 g
INACTIVE INGREDIENTS: WATER; DIETHYLENE GLYCOL MONOETHYL ETHER; PROPYLENE GLYCOL; BUTYLENE GLYCOL; LACTIC ACID; DEXTROSE; GLYCERYL MONOSTEARATE; DICAPRYLYL CARBONATE; CETOSTEARYL ALCOHOL; SODIUM CETOSTEARYL SULFATE; GLYCERIN; ALOE VERA LEAF; HAMAMELIS VIRGINIANA TOP; POLYOXYL 20 CETOSTEARYL ETHER; CYCLOMETHICONE; CHAMOMILE; TROLAMINE ; METHYLPARABEN; POLYSORBATE 80; PROPYLPARABEN

SPAI-SONS MARIGOLD CREAM / CREMA DE CALENDULA

ACTIVE INGREDIENT

SPAI-SONS MARIGOLD CREAM IS BASED IN CALENDULA OFFICINALIS EXTRACT

PURPOSE

THE PRODUCT HAS BEEN DEVELOPED TO IMPLEMENT IN AREAS WHERE THIS FLASH, USEFUL IN WOUND HEALING PROCESS

KEEP OUT OF REACH OF CHILDREN

THIS PRODUCT KEEP OUT OF REACH OF THE CHILDREN

INDICATIONS AND USAGE

THIS PRODUCTT MAY BE USED IN PEOPLE WHO DO NOT SUBMIT HYPERSENSITIVITY COMPONENTS, CAN BE USED AS A DAILY MOISTURIZING SKIN

WARNINGS

AVOID IN TAKE OF PRODUCT, IF SO CHECK WITH YOUR DOCTOR

DOSAGE AND ADMINISTRATION

THE PRODUCT IS TOPICAL APPLICATION, APPLY THE AMOUNT NEEDED IN THE AREA DESIRED

INACTIVE INGREDIENT

THE EXCIPIENTS CONTAINED IN THIS PRODCUT ARE PART OF A FORMULATION BASE ON A MOISTURIZER AND CONDITIONING THE SKIN, WHICH DOES NOT GENERATE IRRITATION, SO ITS USE IS NOT CONTRAINDICATED.
ALSO CALENDULA OFFICINALIS EXTRACT HAS OTHER NATURAL EXTRACTS THAT HELP GIVE A BETTER FEELING IN THE SKIN.

IMAGE OF THE CARTON LABEL